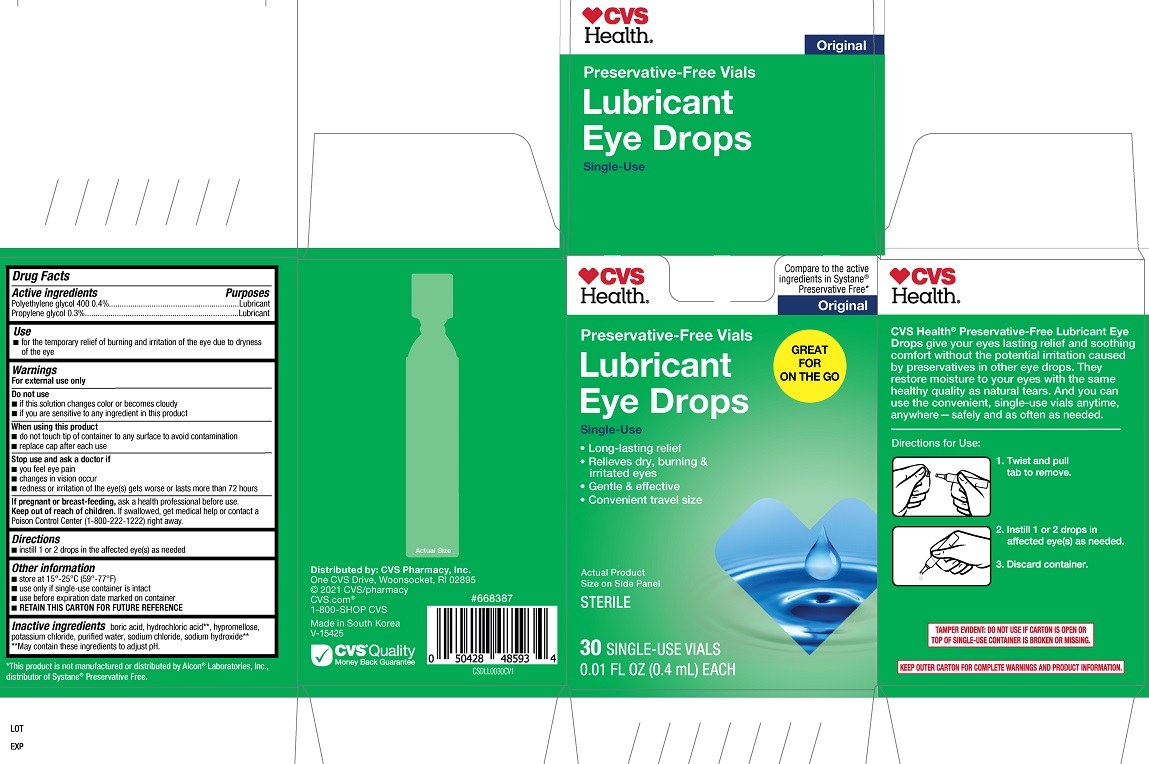 DRUG LABEL: CVS Lubricant Eye Drops Original
NDC: 69842-746 | Form: SOLUTION
Manufacturer: CVS
Category: otc | Type: HUMAN OTC DRUG LABEL
Date: 20251230

ACTIVE INGREDIENTS: POLYETHYLENE GLYCOL 400 0.4 g/100 mL; PROPYLENE GLYCOL 0.3 g/100 mL
INACTIVE INGREDIENTS: HYDROCHLORIC ACID; SODIUM HYDROXIDE; WATER; BORIC ACID; HYPROMELLOSE, UNSPECIFIED; POTASSIUM CHLORIDE; SODIUM CHLORIDE

CVS Lubricant Eye Drops Original 30 ct. (PLD)

Active ingredients

Polyethylene glycol 400.....0.4%
Propylene glycol.................0.3%

Purposes

Polyethylene glycol 400....Lubricant
Propylene glycol................Lubricant

Use

- for the temporary relief of burning and irritation of the eye due to dryness of the eye

Warnings

For external use only

Do not use

- if this solution changes or becomes cloudy
- if you are sensitive to any ingredient in this product

When using this product

- do not touch tip of container to any surface to avoid contamination
- replace cap after each use

Stop use and ask a doctor if

- you feel eye pain
- changes in vision occur
- redness or irritation of the eye(s) gets worse or lasts more than 72 hours

PREGNANCY OR BREAST FEEDING

If pregnant or breast-feeding, ask a health professional before use.

Keep out of reach of children. If swallowed get medical help or contact a Poison Control Center (1-800-222-1222) right away.

Directions

- instill 1 or 2 drops in the affected eye(s) as needed

Other information

- store at 15º-25º (59º-77 F)
- use only if single-use container is intact
- use before expiration date marked on container
- RETAIN THIS CARTON FOR FUTURE REFERENCE

Inactive ingredients

boric acid, hydrochloric acid**, hypromellose, potassium chloride, purified water, sodium chloride, sodium hydroxide**

**May contain these ingredients to adjust pH.